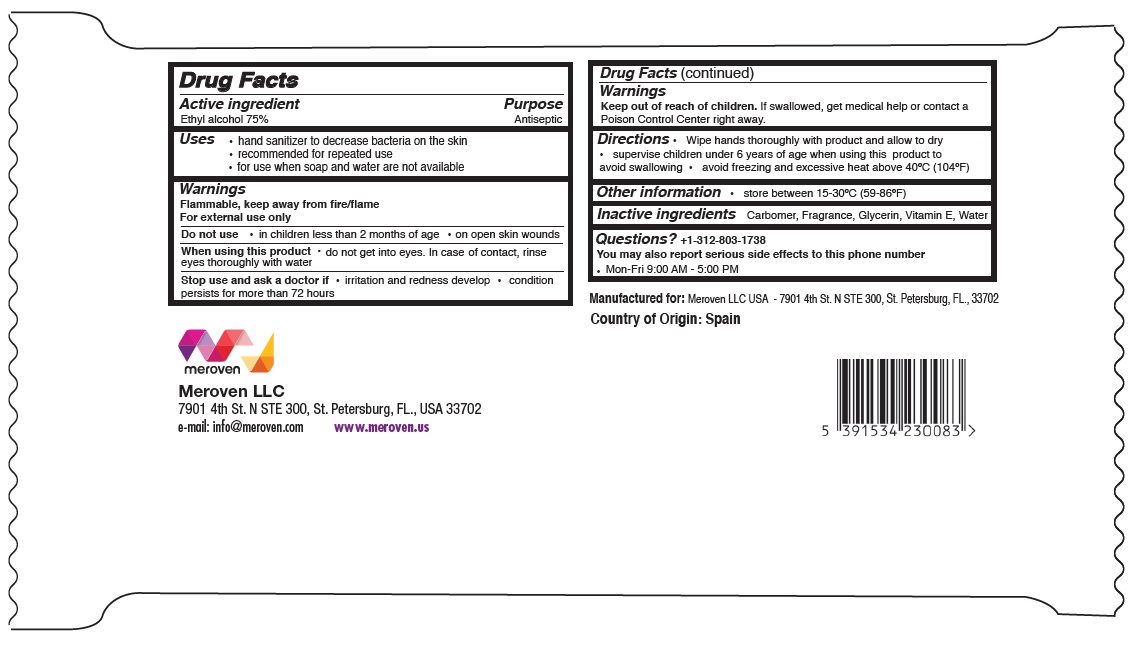 DRUG LABEL: Micro Guard Hand Sanitizer Wipes
NDC: 74653-201 | Form: CLOTH
Manufacturer: Meroven Llc
Category: otc | Type: HUMAN OTC DRUG LABEL
Date: 20200514

ACTIVE INGREDIENTS: ALCOHOL 75 mL/100 mL
INACTIVE INGREDIENTS: CARBOMER HOMOPOLYMER, UNSPECIFIED TYPE; GLYCERIN; .ALPHA.-TOCOPHEROL; WATER

Micro Guard Antiseptic Hand Sanitizer Wipes

Active ingredient

Ethyl alcohol 75%

Purpose

Antiseptic

INDICATIONS AND USAGE

Uses • hand sanitizer to decrease bacteria on the skin
• recommended for repeated use

• for use when soap and water are not available

Warnings

Flammable, keep away from fire/flame

For external use only

Do not use • in children less than 2 months of age • on open skin wounds

When using this product • do not get into eyes. In case of contact, rinse eyes thoroughly with water

Stop use and ask a doctor if • irritation and redness develop • condition persists for more than 72 hours

Keep out of reach of children. If swallowed, get medical help or contact a Poison Control Center right away.

DOSAGE AND ADMINISTRATION

Directions • Wipe hands thoroughly with product and allow to dry • supervise children under 6 years of age when using this product to avoid swallowing • avoid freezing and excessive heat above 40ºC (104ºF)

Other information • store between 15-30ºC (59-86ºF)

Inactive ingredients Carbomer, Fragrance, Glycerin, Vitamin E, Water

Questions? +1-312-803-1738
You may also report serious side effects to this phone number

. Mon-Fri 9:00 AM - 5:00 PM

e-mail: info@meroven.com www.meroven.us

Manufactured for: Meroven LLC USA - 7901 4th St. N STE 300, St. Petersburg, FL., 33702
Country of Origin: Spain